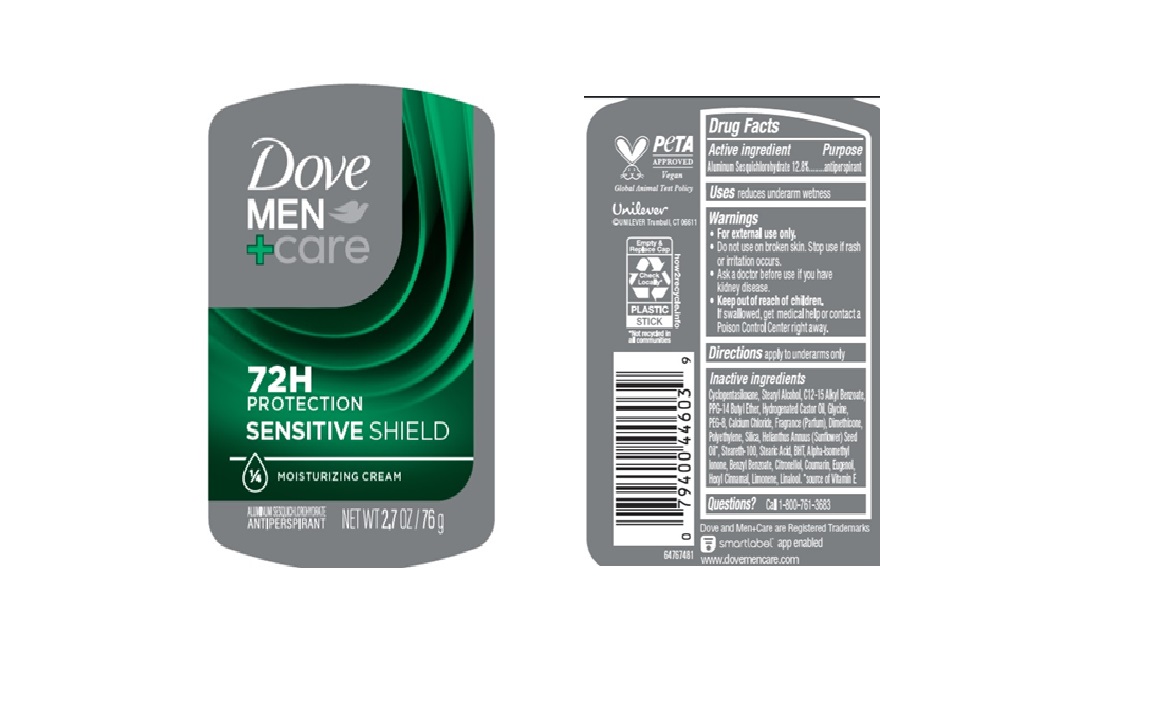 DRUG LABEL: Dove
NDC: 64942-2361 | Form: STICK
Manufacturer: Conopco d/b/a/ Unilever
Category: otc | Type: HUMAN OTC DRUG LABEL
Date: 20250331

ACTIVE INGREDIENTS: ALUMINUM SESQUICHLOROHYDRATE 12.8 g/100 g
INACTIVE INGREDIENTS: SILICA; STEARETH-100; BENZYL BENZOATE; EUGENOL; PPG-14 BUTYL ETHER; ALPHA-ISOMETHYL IONONE; HEXYL CINNAMAL; DIMETHICONE; HELIANTHUS ANNUUS (SUNFLOWER) SEED OIL; BHT; LINALOOL, (+/-)-; HYDROGENATED CASTOR OIL; GLYCINE; POLYETHYLENE; STEARIC ACID; CITRONELLOL; C12-15 ALKYL BENZOATE; PEG-8; CALCIUM CHLORIDE; LIMONENE, (+)-; CYCLOPENTASILOXANE; STEARYL ALCOHOL; COUMARIN

Dove Men + Care Sensitive Shield 72H Antiperspirant

DESCRIPTION

Dove Men + Care Sensitive Shield 72H Antiperspirant

ACTIVE INGREDIENT

Aluminum Sesquichlorohydrate (12.8%)

PURPOSE

antiperspirant

INDICATIONS AND USAGE

reduces underarm wetness

WARNINGS

For external use only.

Do not use on broken skin.

Stop use if rash or irritation occurs.

Ask a doctor before use if you have kidney disease.

Keep out of reach of children. If swallowed, get medical help or contact a Poison Control Center right away.

DOSAGE AND ADMINISTRATION

apply to underarms only

INACTIVE INGREDIENT

Cyclopentasiloxane, Stearyl Alcohol, C12-15 Alkyl Benzoate, PPG-14 Butyl Ether, Hydrogenated Castor Oil, Glycine, PEG-8, Calcium Chloride, Fragrance (Parfum), Dimethicone, Polyethylene, Silica, Helianthus Annuus (Sunflower) Seed Oil, Steareth-100, Stearic Acid, BHT, Alpha-Isomethyl Ionone, Benzyl Benzoate, Citronellol, Coumarin, Eugenol, Hexyl Cinnamal, Limonene, Linalool.

QUESTIONS

Call 1-800-761-3683